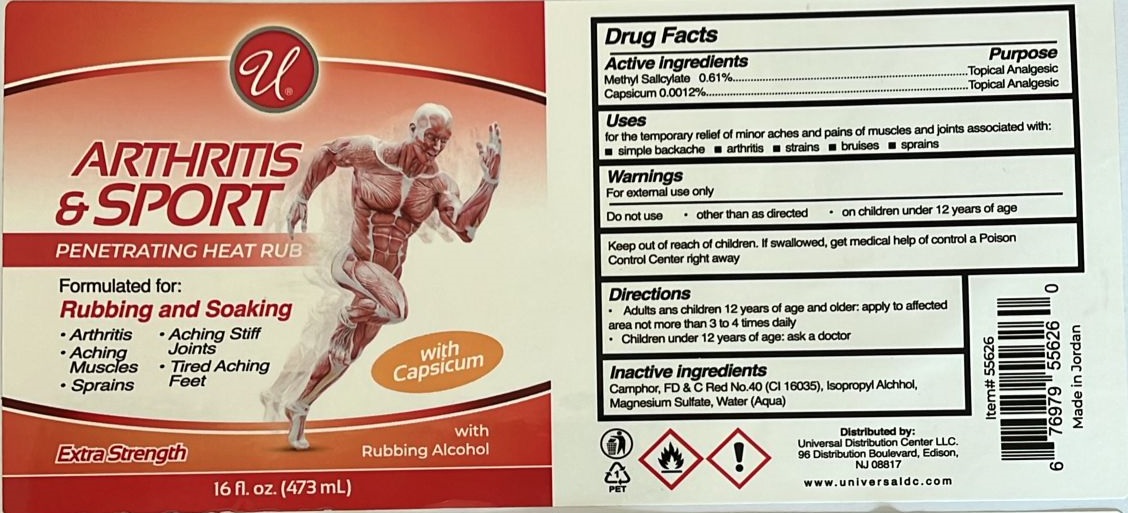 DRUG LABEL: Universal ARTHRITIS and SPORT
NDC: 52000-303 | Form: LIQUID
Manufacturer: Universal Distribution Center LLC
Category: otc | Type: HUMAN OTC DRUG LABEL
Date: 20241122

ACTIVE INGREDIENTS: METHYL SALICYLATE 0.61 g/100 mL; CAPSICUM 0.0012 g/100 mL
INACTIVE INGREDIENTS: CAMPHOR (NATURAL); FD&C RED NO. 40; ISOPROPYL ALCOHOL; MAGNESIUM SULFATE, UNSPECIFIED FORM; WATER

Universal ARTHRITIS & SPORT

Active ingredients

Methyl Salicylate 0.61%

Capsicum 0.0012%

Purpose

Topical Analgesic

Uses

for the temporary relief of minor aches and pains of muscles and joints associated with:

• simple backache • arthritis • strains • bruises • sprains

Warnings

For external use only

Do not use • other than as directed • on children under 12 years of age

Keep out of reach of children. If swallowed, get medical help or contact a Poison Control Center right away.

Directions

• Adults and children 12 years of age and older: apply to affected area not more than 3 to 4 times daily

• Children under 12 years of age: ask a doctor

Inactive ingredients

Camphor, FD & C Red No.40 (CI 16035), Isopropyl Alcohol, Magnesium Sulfate, Water (Aqua)

PENETRATING HEAT RUB

Formulated for:

Rubbing and Soaking

• Arthritis • Aching Stiff Joints
• Aching Muscles • Tired Aching Feet • Sprains

Extra Strength

with Rubbing Alcohol

Distributed by:Universal Distribution Center LLC.
96 Distribution Boulevard, Edison,
NJ 08817

www.universaldc.com

Made in Jordan